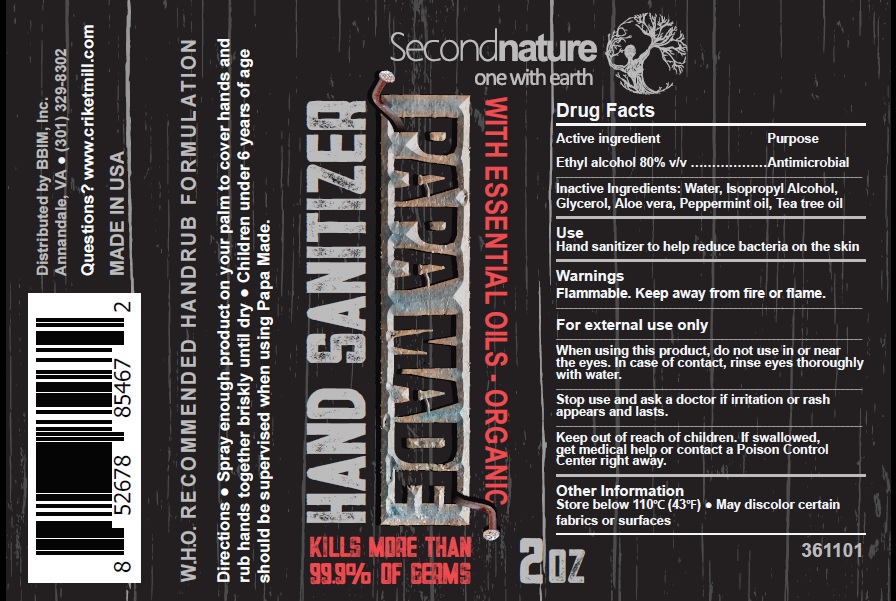 DRUG LABEL: PAPA MADE
NDC: 73709-001 | Form: LIQUID
Manufacturer: BBIM INC
Category: otc | Type: HUMAN OTC DRUG LABEL
Date: 20200317

ACTIVE INGREDIENTS: ALCOHOL 80 mL/100 mL
INACTIVE INGREDIENTS: GLYCERIN; ALOE VERA LEAF; PEPPERMINT OIL; TEA TREE OIL; WATER; ISOPROPYL ALCOHOL

Drug Facts

Active ingredient

Ethyl alcohol 80% v/v

Purpose

Antimicrobial

Uses

Hand sanitizer to help reduce bacteria on the skin.

Warnings

Flammable, keep away from fire or flame

For external use only

When using this product

- do not use in or near the eyes
- in case of contact, rinse eyes thoroughly with water

Stop use and ask a doctor

if irritation or rash appears and lasts

Keep out of reach of children.

If swallowed, get medical help right away or contact a Poison Control Center right away.

Directions

- spray enough product on your palm to cover hands and rub hands together briskly until dry.
- children under 6 years of age should be supervised when using Papa Made.

Other information

- Store below 110^0C (43^0F).
- May discolor certain fabrics or surfaces

Inactive ingredient

Water, Isopropyl Alcohol, Glycerol, Aloe vera, Peppermint oil, Tea tree oil